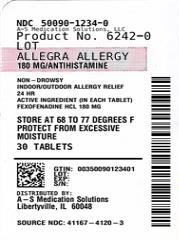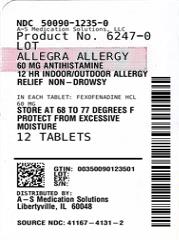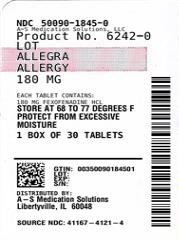 DRUG LABEL: ALLEGRA ALLERGY
NDC: 50090-1234 | Form: TABLET, FILM COATED
Manufacturer: A-S Medication Solutions
Category: otc | Type: HUMAN OTC DRUG LABEL
Date: 20240730

ACTIVE INGREDIENTS: FEXOFENADINE HYDROCHLORIDE 180 mg/1 1
INACTIVE INGREDIENTS: SILICON DIOXIDE; CROSCARMELLOSE SODIUM; HYPROMELLOSE, UNSPECIFIED; MAGNESIUM STEARATE; MICROCRYSTALLINE CELLULOSE; POLYETHYLENE GLYCOL, UNSPECIFIED; POVIDONE, UNSPECIFIED; STARCH, CORN; TITANIUM DIOXIDE; BROWN IRON OXIDE

ALLEGRA ALLERGY

Allegra Allergy

Allegra Allergy® - 12/24 HOUR

Drug Facts

Active ingredient

(in each tablet)
12 Hour Tablet: Fexofenadine HCl 60 mg

24 Hour Tablet: Fexofenadine HCl 180 mg

Purpose

Antihistamine

Uses

temporarily relieves these symptoms due to hay fever or other upper respiratory allergies:

- runny nose
- sneezing
- itchy, water eyes
- itching of the nose or throat

Warnings

Do not use

if you have ever had an allergic reaction to this product or any of its ingredients

Ask a doctor before use if you have

kidney disease. Your doctor should determine if you need a different dose.

When using this product

- do not take more than directed
- do not take at the same time as aluminum or magnesium antacids
- do not take with fruit juices (see Directions)

Stop use and ask a doctor if

an allergic reaction to this product occurs. Seek medical help right away.

If pregnant or breast-feeding,

ask a health professional before use.

Keep out of reach of children.

In case of overdose, get medical help or contact a Poison Control Center right away.

Allegra 12 Hour Directions

adults and children 12 years of age and over | take one 60 mg tablet with water every 12 hours; do not take more than 2 tablets in 24 hours
children under 12 years of age | do not use
adults 65 years of age and older | ask a doctor
consumers with kidney disease | ask a doctor

Allegra 24 Hour Directions

adults and children 12 years of age and over | take one 180 mg tablet with water once a day; do not take more than 1 tablet in 24 hours
children under 12 years of age | do not use
adults 65 years of age and older | ask a doctor
consumers with kidney disease | ask a doctor

Other information

- safety sealed: do not use if carton is opened or if individual blister units are torn or opened or if inner foil seal on bottle is torn or missing
- store between 20° and 25°C (68° and 77°F)
- protect from excessive moisture

Inactive ingredients

colloidal silicon dioxide, croscarmellose sodium, hypromellose, iron oxide blends, magnesium stearate, microcrystalline cellulose, polyethylene glycol, povidone, pregelatinized starch, titanium dioxide

Questions or comments?

call toll-free 1-800-633-1610 or www.allegra.com

HOW SUPPLIED

Product: 50090-1234

NDC: 50090-1234-0 30 TABLET, FILM COATED in a BOTTLE, PLASTIC / 1 in a CARTON

Product: 50090-1235

Product: 50090-1845